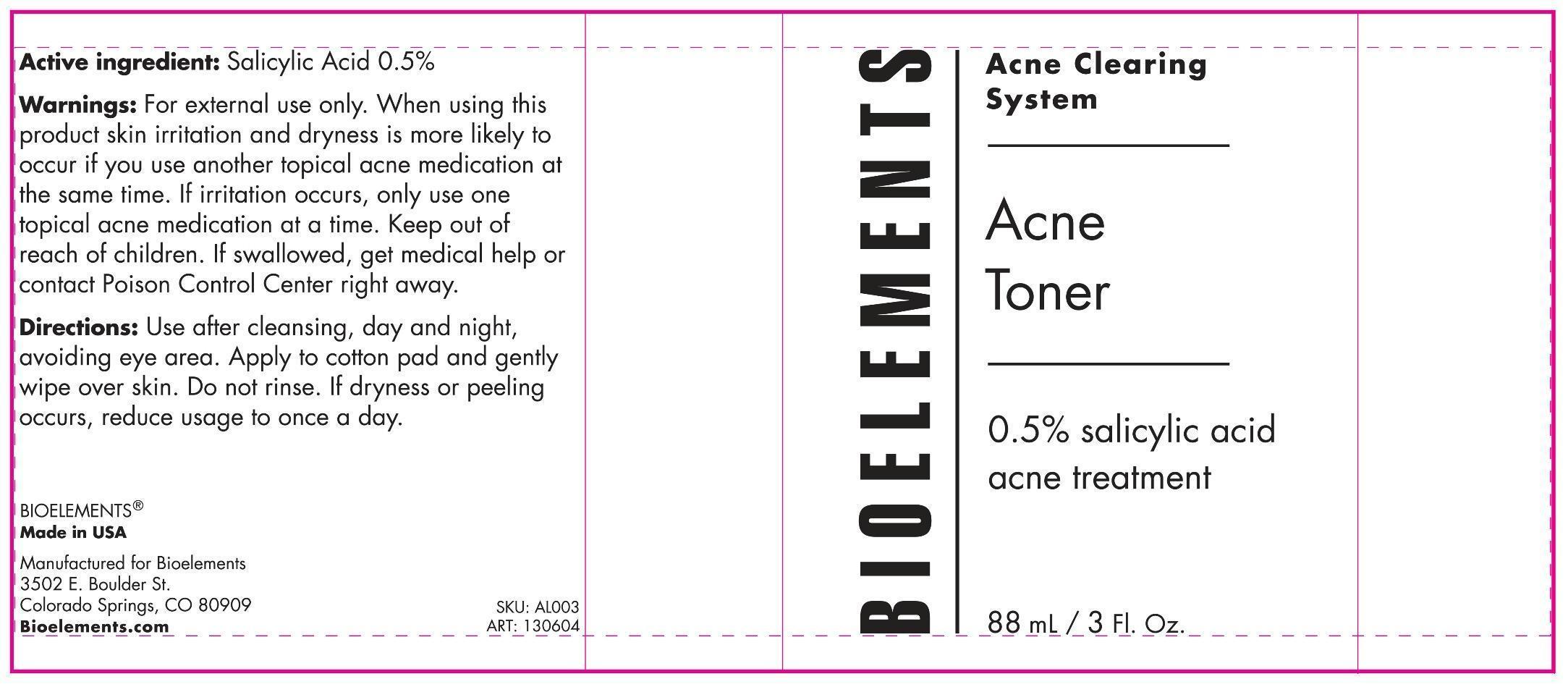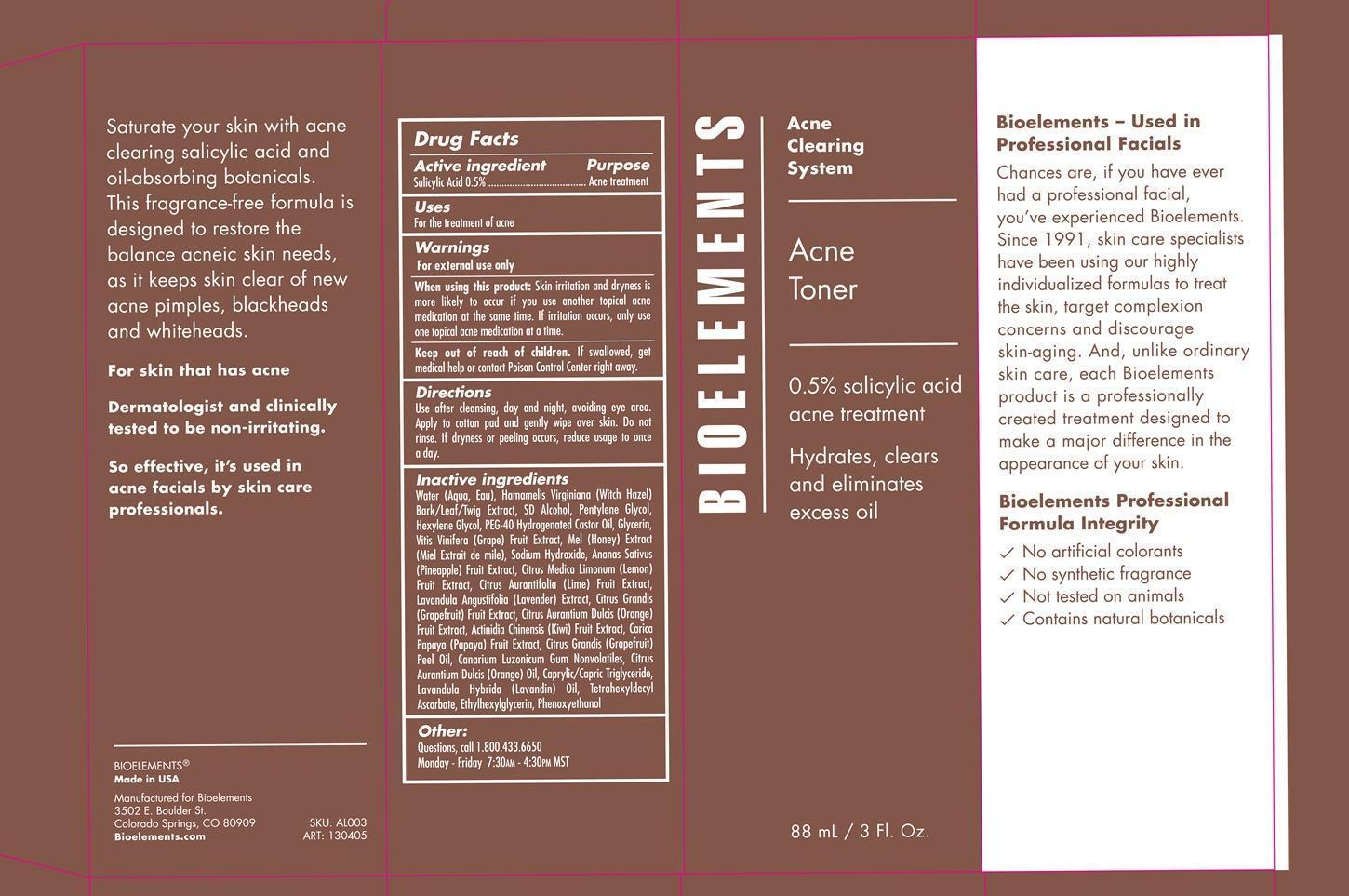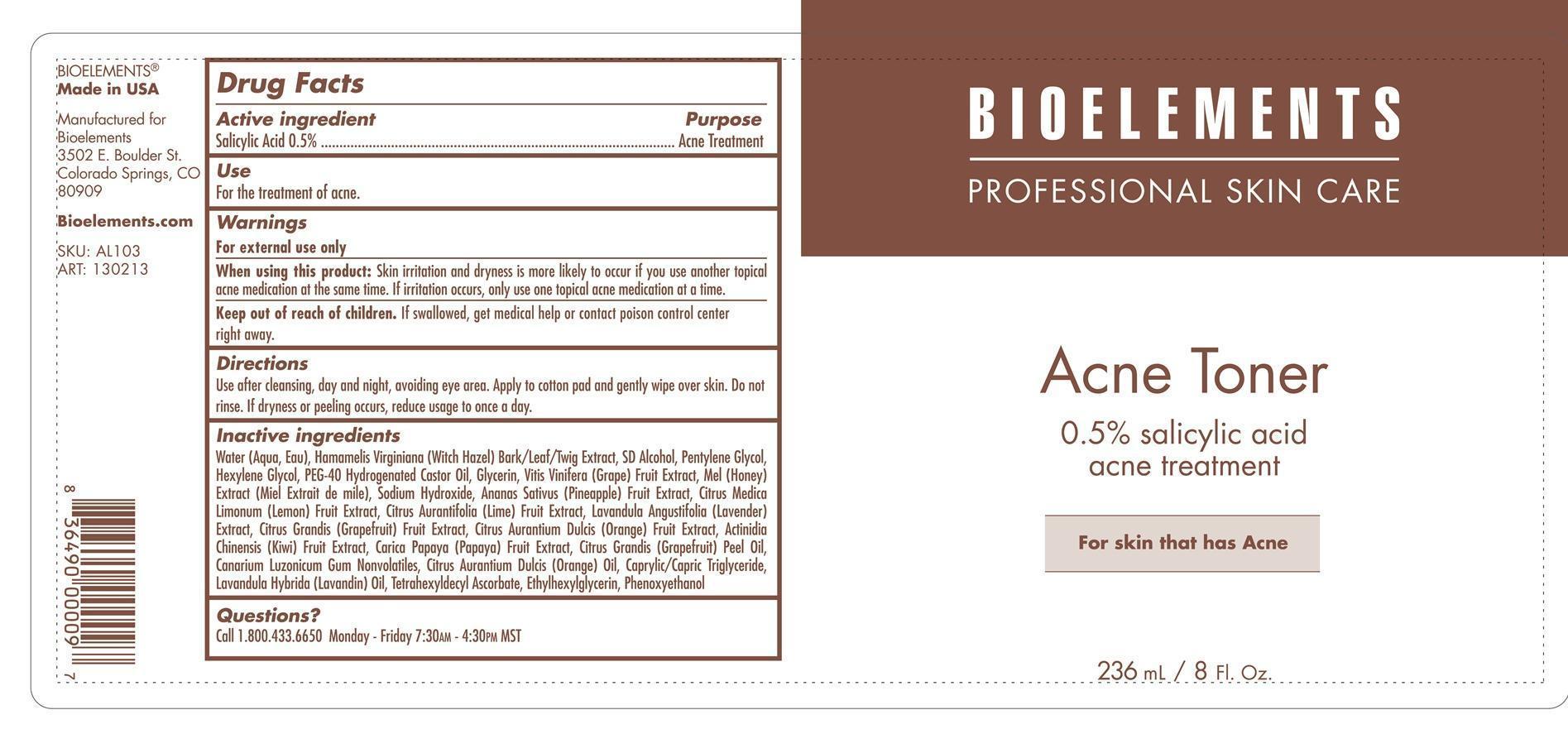 DRUG LABEL: Acne Toner
NDC: 49825-130 | Form: CREAM
Manufacturer: Bioelements, Inc.
Category: otc | Type: HUMAN OTC DRUG LABEL
Date: 20130618

ACTIVE INGREDIENTS: SALICYLIC ACID 0.5 g/100 mL
INACTIVE INGREDIENTS: WATER; HAMAMELIS VIRGINIANA LEAF; PENTYLENE GLYCOL; HEXYLENE GLYCOL; GLYCERIN; WINE GRAPE; HONEY; SODIUM HYDROXIDE; PINEAPPLE; LEMON; LIME (CITRUS); LAVANDULA ANGUSTIFOLIA FLOWER; GRAPEFRUIT; ORANGE; KIWI FRUIT; PAPAYA; GRAPEFRUIT OIL; ELEMI; ORANGE OIL; MEDIUM-CHAIN TRIGLYCERIDES; LAVANDIN OIL; TETRAHEXYLDECYL ASCORBATE; ETHYLHEXYLGLYCERIN; PHENOXYETHANOL

Acne Toner

Active ingredient Purpose

Salicylic Acid 0.5% Acne treatment

Uses

For the treatment of acne

Keep out of reach of children. If swallowed get medical help or contact Poison Control Center right away.

When using this product: Skin irritation and dryness is more likely to occur if you use another topical acne medication at the same time. If irritation occurs, only use one topical acne medication at a time.

warnings

For external use only

Directions

Use after cleansing, day and night, avoiding eye area. Apply to cotton pad and gently wipe over skin. Do not rinse. If dryness or peeling occurs, reduce usage to once a day.

Inactive ingredients

Water (Aqua, Eau), Hamamelis Virginiana (Witch Hazel) Bark/Leaf/Twig Extract, SD Alcohol, Pentylene Glycol, Hexylene Glycol, PEG-40 Hydrogenated Castor Oil, Glycerin, Vitis Vinifera (Grape) Fruit Extract, Mel (Honey) Extract (Miel Extrait de mile), Sodium Hydroxide, Ananas Sativus (Pineapple) Fruit Extract, Citrus Medica Limonium (Lemon) Fruit Extract, Citrus Aurantifolia (Lime) Fruit Extract, Lavandula Angustifolia(Lavender) Extract, Citrus Grandis (Grapefruit) Fruit Extract, Citrus Aurantium Dulcis (Orange) Fruit Extract, Actinidia Chinensis (Kiwi) Fruit Extract, Carica Papaya (Papaya) Fruit Extract, Citrus Grandis (Grapefruit) Peel Oil, Canarium Luzonicum Gum Nonvolatiles, Citrus Aurantium Dulcis (Orange) Oil, Caprylic/Capric Triglyceride, Lavandula Hybrida (Lavandin) Oil, Tetrahexyldecyl Ascorbate, Ethylhexylglycerin, Phenoxyethanol.

PACKAGE LABEL

Biolelements

Acne Clearing System

Acne Toner

0.5% salicylic acid acne treatment

Hydrates, clears and eliminates excess oil

88 mL / 3 Fl Oz